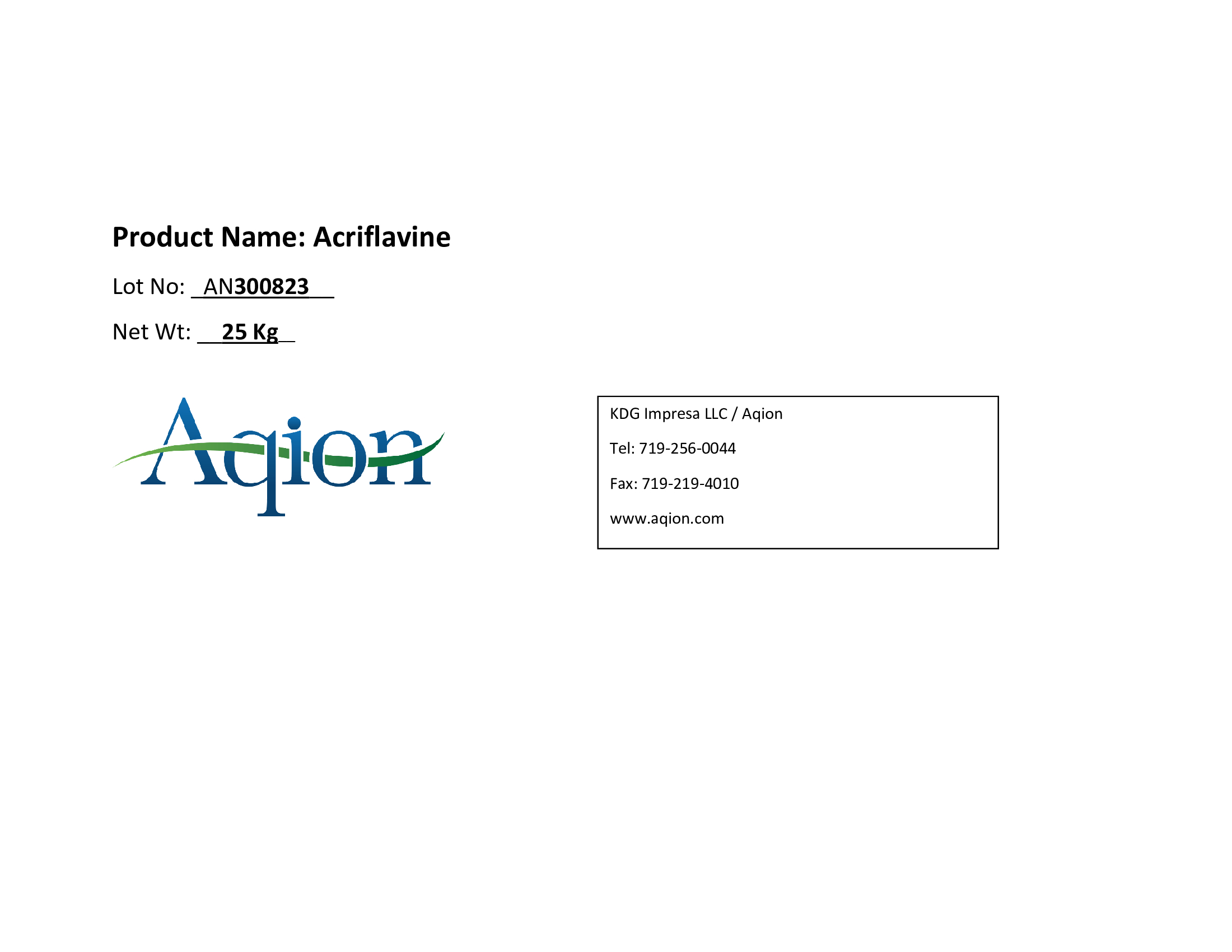 DRUG LABEL: Acriflavine
NDC: 43457-651 | Form: POWDER
Manufacturer: KDG Impresa LLC, Aqion
Category: other | Type: BULK INGREDIENT - ANIMAL DRUG
Date: 20231128

ACTIVE INGREDIENTS: ACRIFLAVINE 1 kg/1 kg

Acriflavine